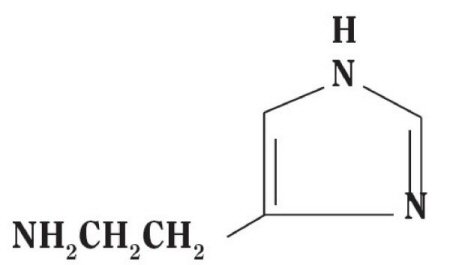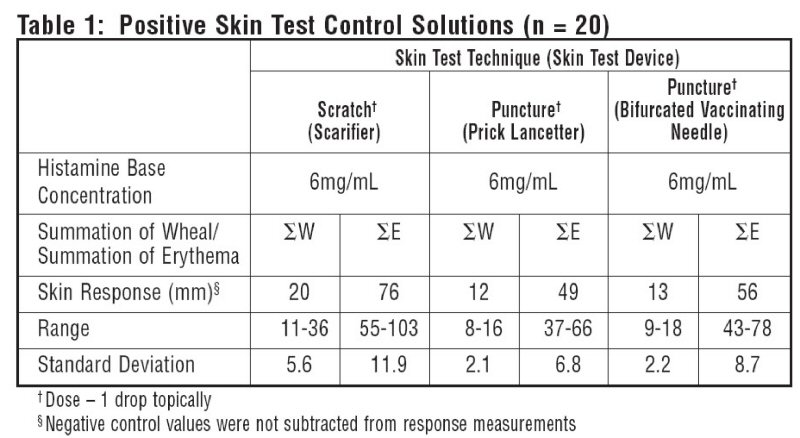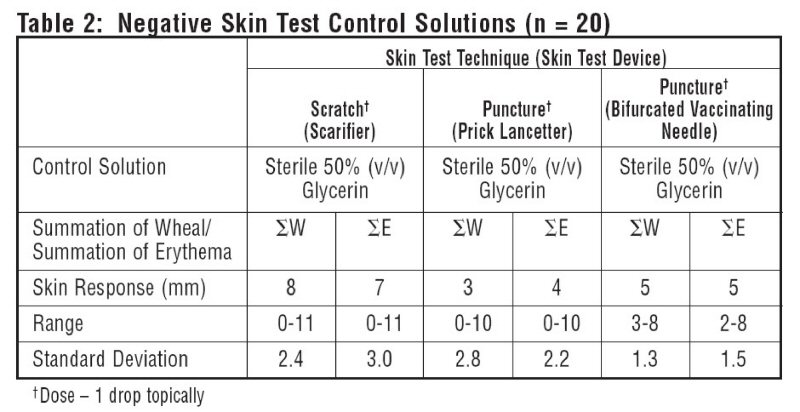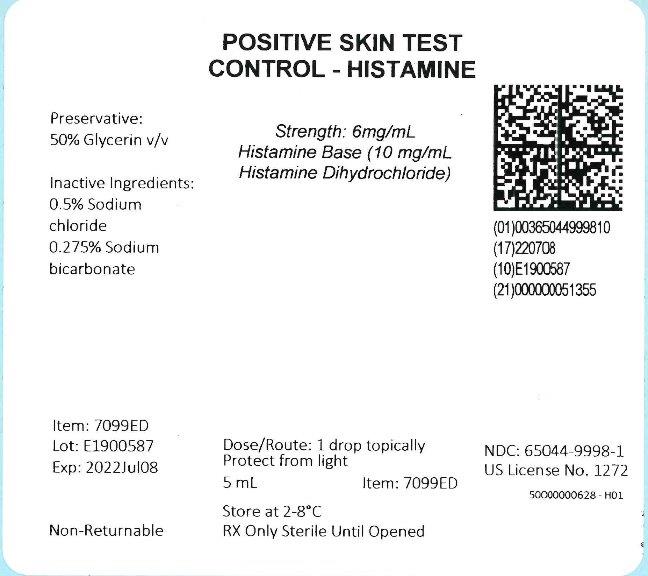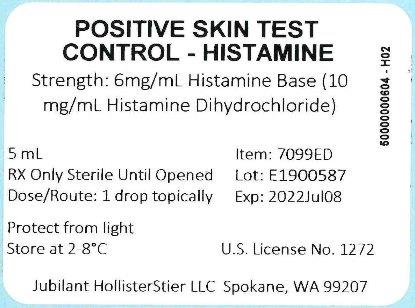 DRUG LABEL: Positive Skin Test Control - Histamine
NDC: 65044-9998 | Form: INJECTION
Manufacturer: Jubilant HollisterStier LLC
Category: prescription | Type: HUMAN PRESCRIPTION DRUG LABEL
Date: 20251119

ACTIVE INGREDIENTS: HISTAMINE 6 mg/1 mL
INACTIVE INGREDIENTS: SODIUM CHLORIDE; SODIUM BICARBONATE; GLYCERIN

Histamine 366140-H05 Initial Upload to Intagras SPL Portal

POSITIVE SKIN TEST CONTROL - HISTAMINE

For Percutaneous (Scratch, Prick or Puncture) Administration
Histamine Base: 6mg/mL
(Histamine Dihydrochloride: 10mg/mL)
This product is to be used by a physician or under the supervision of a physician.

DESCRIPTION

Histamine Dihydrochloride contains histamine, a potent vasodilator having the chemical name 2-(4-Imidazolyl) ethylamine. Histamine has an empirical formula of C5H9N3, a molecular weight of 111.15, and the following chemical structure:

Histamine Dihydrochloride is available in the following strengths:
1. SCRATCH, PRICK or PUNCTURE TEST CONTROL:
Positive Skin Test Control - Histamine contains 6.0 mg/mL Histamine Base and is a clear, colorless, sterile solution. It consists of Histamine Dihydrochloride 10mg/mL, Sodium Chloride 0.5%, Sodium Bicarbonate 0.275%, and Glycerin 50.0% (v/v) as a preservative.

CLINICAL PHARMACOLOGY

Pharmacological actions of histamine include the increase of capillary and post capillary venular permeability. This vascular change leads to the wheal-flare response. Large reactions can cause an amplification of a reaction to a nearby skin test. Histamine is degraded either by oxidative deamination or by methylation and oxidative deamination so that the principal excretion products are imidazoleacetic acid-riboside and 1-methyl imidazoleacetic acid respectively.2

10 atopic subjects and 10 non-atopics were tested with Positive Skin Test Control - Histamine Solutions, and two negative control solutions. Thirteen females (35-49 years old; mean age 36.5) and 7 males (23-45 years old; mean age 36.4) were tested. This study included 19 Caucasian subjects and 1 African American subject. Different skin test devices produce different skin test responses. (14,15) Study results are summarized in Table 1 and Table 2. Atopic and non-atopic subject information was combined, as there were no significant differences in their skin responses.

Summation of wheal (∑W) or summation of erythema (∑E) was determined by measuring the longest diameter and the mid-point orthoganol diameter of the wheal or erythema response and summing the two measurements.

Malling tested 25 subjects using a straight needle prick technique with Histamine Dihydrochloride 10mg/mL and found wheal single diameters of 5.4-8.5mm (mean 7 mm). 13

Histamine Dihydrochloride at 10mg/mL has been shown to elicit fewer false negative and false positive reactions than Histamine Dihydrochloride at 1mg/mL. 12 10mg/mL Histamine Dihydrochloride has been shown to be the appropriate strength to perform biological standardization using skin reactivity to histamine as a standard of comparison.11,13

INDICATIONS AND USAGE

Positive Skin Test Control - Histamine is indicated as an adjunct in allergy skin test for diagnosis, as a positive control to test wheal-flare response of skin for evaluation of skin test response to allergenic extracts.

CONTRAINDICATIONS

Positive Skin Test Control - Histamine is contraindicated in patients with a history of hypersensitivity to histamine products, and in patients with hypotension, severe hypertension, vasomotor instability, severe cardiac, pulmonary or renal disease.

WARNINGS

Attacks of severe asthma or other serious allergic conditions may be precipitated by the administration of Histamine Dihydrochloride in patients with bronchial disease. Caution is advised in using histamine in such patients and in those with a history of bronchial asthma. Histamine Dihydrochloride has not been approved for unlabeled use as gastric acid stimulus or for detecting bronchial hyperactivity.

PRECAUTIONS

GENERAL PRECAUTIONS

(1) General: It is necessary that scarifiers, syringes, and needles be properly sterilized before use on each patient to prevent the possibility of accidental transfer of serum hepatitis and other infectious agents from one person to another. Disposable products may also be used.
Always have injectable epinephrine and a tourniquet available when any skin tests are being made. (See ADVERSE REACTIONS Section)
Patients should be observed in the office for 30 minutes after administration of the test and instructed to return to the office promptly if symptoms of an allergic reaction or shock occur.

DRUG INTERACTIONS

(2) Drug Interactions: Certain medications may lessen the skin test wheal and erythema responses elicited by histamine for varying time periods. Conventional antihistamines should be discontinued at least 5 days before skin testing. Long acting antihistamines should be discontinued for at least 3 weeks prior to skin testing.7 Topical steroids should be discontinued at the skin test site for at least 2-3 weeks before skin testing.7,8

Tricyclic antidepressants such as Doxepin should be withheld for at least 7 days before skin testing.9 The physician must determine whether the risk of severe depression occurring in patients who discontinue their medication outweighs the benefits that could be obtained from skin testing. Topical local anesthetics may suppress the flare responses and should be avoided in skin test sites.10

CARCINOGENESIS AND MUTAGENESIS AND IMPAIRMENT OF FERTILITY

(3) Carcinogenesis, Mutagenesis, Impairment of Fertility: Studies have not been performed on Positive Skin Test Control-Histamine.

PREGNANCY

(4) Pregnancy: Positive Skin Test Control-Histamine. Animal reproduction studies have not been conducted on Histamine Dihydrochloride. It is also not known whether Histamine Dihydrochloride can cause fetal harm when administered to a pregnant woman or can affect reproduction capacity. Histamine Dihydrochloride should be given to a pregnant woman only if clearly needed.

NURSING MOTHERS

(5) Nursing Mothers: It is unknown whether Histamine Dihydrochloride affects lactation or is excreted in human milk. Because many drugs are excreted in human milk, caution should be exercised when Positive Skin Test Control-Histamine is administered to a nursing woman.

PEDIATRIC USE

(6) Pediatric Use: Indications and dosage for the pediatric population are the same as for adults; however, the reactions to histamine are smaller. Studies have shown that the use of histamine solutions for skin test is safe in infants and young children.4,5,6

ADVERSE REACTIONS

Large doses of histamine may precipitate systemic reactions. These reactions may include flushing, dizziness, headache, bronchial constriction, urticaria, asthma, marked hypotension or hypertension, abdominal cramps, vomiting, metallic taste, local or generalized allergic manifestations.

An antihistamine preparation may be given orally, I.M. or I.V. to prevent or ameliorate systemic reactions to the drug.

If a systemic or anaphylactic reaction does occur, apply a tourniquet above the site of injection and inject 1:1000 epinephrine-hydrochloride intramuscularly or subcutaneously into the opposite arm. Loosen the tourniquet at least every 10 minutes. Do not obstruct arterial blood flow with the tourniquet.

Epinephrine Dosage:
ADULT: 0.3 to 0.5 mL should be injected. Repeat in 5 to 10 minutes if necessary.
PEDIATRIC: The usual initial dose is 0.01 mg (mL) per kg body weight or 0.3 mg(mL) per square meter of body surface area. Suggested dosage for infants to 2 years of age is 0.05 mL to 0.1 mL; for children 2 to 6 years, 0.15 mL; and children 6 to 12 years, 0.2 mL. Single pediatric doses should not exceed 0.3 mg (mL). Doses may be repeated as frequently as every 20 minutes, depending on the severity of the condition and the response of the patient.

After administration of epinephrine, profound shock or vasomotor collapse should be treated with intravenous fluids, and possibly vasoactive drugs. Oxygen should be given by mask. Aminophylline or adrenal corticosteroids may be used if necessary after adequate epinephrine and circulatory support has been given.

Emergency resuscitation measures and personnel trained in their use should be available immediately in the event of a serious systemic or anaphylactic reaction not responsive to the above measures (Ref. J. ALLERGY AND CLINICAL IMMUNOLOGY 77s (2): p. 271-273, 1986).16

Rarely are all of the above measures necessary, the tourniquet and epinephrine usually producing prompt responses. However, the physician should be prepared in advance for all contingencies. Promptness in beginning emergency treatment measures is of utmost importance.

Adverse Event Reporting
Report all adverse events to Jubilant HollisterStier LLC Customer Technical Services Department at 1 (800) 992-1120. A voluntary adverse event reporting system for health professionals is available through the FDA MEDWATCH program. Preprinted forms (FDA Form 3500) are available from the FDA by calling 1 (800) FDA-1088. Completed forms should be mailed to MEDWATCH, 5600 Fisher Lane, Rockville, MD 20852-9787 or Fax to: 1 (800) FDA-0178.

OVERDOSAGE

Overdosage may cause severe symptoms, including circulatory collapse, shock, and even death. Intravenous administration of histamine in normal volunteers at doses of up to 1.0 µg/kg/min produced flushing, headaches, tachycardia and decreased diastolic blood pressure. 1,2,3
See ADVERSE REACTIONS Section for emergency treatment steps.

DOSAGE AND ADMINISTRATION

(1) General

Parenteral drug products should be inspected visually for particulate matter and discoloration prior to administration, whenever solution and container permit. Prior to testing, clean the skin area with ether or alcohol and allow to dry. The back or the volar surface of the arms are the most satisfactory sites for testing.

Skin of the posterior thighs or abdomen may be used if necessary. Avoid very hairy areas where possible, since the reactions will be smaller and more difficult to interpret there. The most satisfactory areas of the back are from the posterior axillary fold to 2.5 cm from the spinal column, and from the top of the scapula to the lower rib margins. The best areas of the arms are the volar surfaces from the axilla to 2.5 or 5 cm above the wrist, skipping the anti-cubital space.

The histamine test should be applied in the same test area as other allergenic extracts tests, but spaced no closer than 4 to 5 cm from adjacent test sites. Use the same technique or procedure that you use for allergen testing.

The negative control is the diluent used in the extract to be tested (e.g. 50% glycerin, Sterile Albumin Saline with Phenol, Sterile Buffered Saline with Phenol).

With each skin testing method, in order for the reaction to Positive Skin Test Control-Histamine (6 mg/mL Histamine Base) to be considered valid, erythema must be present which exceeds the respective negative control by 4 mm (∑E). A wheal reaction does not have to be elicited unless there is a wheal reaction to the respective negative control. In this case, the wheal of the positive control must exceed the negative control by 4 mm (∑W) in order to be considered appropriate. Record measurement of erythema and wheal diameters.

Tables 1 and 2 summarize skin testing results with histamine base and controls in atopic and non-atopic subjects using four different devices and methods.

(2) Scratch, Prick or Puncture Test: Positive Skin Test Control-Histamine, 6.0 mg/mL Histamine Base.
The Scratch, Prick or Puncture test should be read in 15 minutes. If a large wheal reaction occurs before that time, wipe excess histamine solution from test site.

a) Use a sterile scarifier for each patient.
Hold the scarifier between the thumb and index finger, press the sharp edge of the instrument against the skin and twirl instrument rapidly. The scratch should disrupt the outer layers of epidermis down to the germinal layer, but should not produce immediate oozing of blood. The amount of pressure needed to produce a satisfactory scratch will vary between patients according to the thickness or fragility of their skin.
Apply one drop of Positive Skin Test Control-Histamine to the scratch test site.
b) Prick or Puncture Test: Prick tests are performed by placing a drop of extract on the skin and piercing through the drop into the skin with a slight lifting motion. Puncture tests are performed by placing a drop of extract on the skin and piercing through the drop perpendicular to the skin with a device such as a Prick Lancetter. After about 1 minute the extract may be wiped away with a dry sponge.

HOW SUPPLIED

SCRATCH, PRICK or PUNCTURE TEST: Positive Skin Test Control-Histamine (6.0 mg/mL Histamine Base), 5 mL sterile amber vial with dropper assembly.

STORAGE

Store at 2°- 8°C. Protect from light when not in use.

REFERENCES

1. Lawlor, Glenn Jr., Thomas J. Fischer, ed., Immediate hypersensitivity: approach to diagnosis. Manual of Allergy and Immunology Diagnosis and Therapy. Little Brown and Company, Boston, 19, 95, 1981.

2. Samter, Max, K. Frank Austin, ed.. Histamine and other mediators of allergic reactions. Immunological Diseases. Little, Brown and Company, Boston, pp. 332-335, 1971.

3. Summers, Richard, Robert Sigler, James H. Schelhamer, and Michael Kaliner. Effects of infused histamine on asthmatic and normal subjects: comparison of skin test responses. J. Allergy Clin. Immunol. 67 (6): 456-464, June 1981.

4. Gary, T.N., L.N. Gay. Skin reactions in infants: Susceptibility of the skin of the newborn to positive atopic sensitization, comparison with reaction to histamine. J. Allergy. 5:488, 1934.

5. Kaliner, M., J. H. Shelhamer, and E.A. Ottesen. Effects of infused histamine: Correlation of plasma histamine levels and symptoms. J. Allergy Clin. Immunol. 69 (3): 283-289.

6. Smith, M.A., L.E. Mansfeld, R. deShazo and H.S. Nelson. An evaluation of the pharmacologic inhibition of the immediate and late cutaneous effect to allergen. J. Allergy Clin. Immunol. 65: 188, 1980.

7. Pipkorn, Ulf. Pharmacological influence of anti-allergic medication on In Vivo allergen testing. Allergy. 43: 81-86, 1988.

8. Andersson, M. and U. Pipkorn. Inhibition of the dermal immediate allergic reaction through prolonged treatment with topical glucocorticosteroids. J. Allergy Clinical Immunology. 79(2): 345-349, February 1987.

9. Rao, Kamineni S., et al. Duration of suppressive effect of tricyclic anti-depressants on histamine induced wheal and flare reactions on human skin. J. Allergy Clinical Immunology. 82: 752-757, November 1988.

10. Pipkorn, Ulf, and M. Andersson. Topical dermal anesthesia inhibits the flare but not the wheal response to allergen and histamine in the skin prick test. Clinical Allergy. 17: 307-311, 1987.

11. Harris, R.I., M.A. Stern, H.K. Watson. Dose response curve of allergen and histamine in skin prick tests. Allergy. 43(8): 565-572, 1988.

12. Berkowitz, R.B., D.G. Tinkleman, C. Lutz, et al. Evaluation of the multi test device for immediate hypersensitivity skin testing. J. Allergy Clin. Immunol. 90:979-985, 1992.

13. Malling, H. J. Skin prick testing and the use of histamine references. Allergy. 39:596-601, 1984.

14. Demoly, P., J. Bousquet, J.C. Manderscheid, et al. Precision of skin prick and puncture tests with nine methods. J. Allergy Clin. Immunol. 88(5):758-762, Nov. 1991.

15. Nelson, H.S., D.M. Rosloniec, L.L. McCall, D. Ikle. Comparative performance of five commercial prick skin test devices. J. Allergy Clin. Immunol. 92:750-756, 1993.

16. Personnel and equipment to treat systemic reactions caused by immunotherapy with allergenic extracts. J. Allergy Clin. Immunol. 77(2):271-273, February 1986.